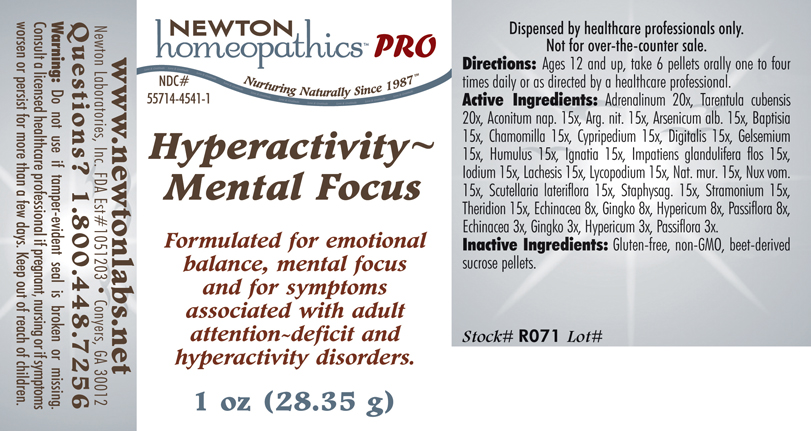 DRUG LABEL: Hyperactivity - Mental Focus 
NDC: 55714-4541 | Form: PELLET
Manufacturer: Newton Laboratories, Inc.
Category: homeopathic | Type: HUMAN PRESCRIPTION DRUG LABEL
Date: 20110601

ACTIVE INGREDIENTS: Epinephrine 20 [hp_X]/1 g; Citharacanthus Spinicrus 20 [hp_X]/1 g; Aconitum Napellus 15 [hp_X]/1 g; Silver Nitrate 15 [hp_X]/1 g; Arsenic Trioxide 15 [hp_X]/1 g; Baptisia Tinctoria 15 [hp_X]/1 g; Matricaria Recutita 15 [hp_X]/1 g; Cypripedium Parvifolum Root 15 [hp_X]/1 g; Digitalis 15 [hp_X]/1 g; Gelsemium Sempervirens Root 15 [hp_X]/1 g; Hops 15 [hp_X]/1 g; Strychnos Ignatii Seed 15 [hp_X]/1 g; Impatiens Glandulifera Flower 15 [hp_X]/1 g; Iodine 15 [hp_X]/1 g; Lachesis Muta Venom 15 [hp_X]/1 g; Lycopodium Clavatum Spore 15 [hp_X]/1 g; Sodium Chloride 15 [hp_X]/1 g; Strychnos Nux-vomica Seed 15 [hp_X]/1 g; Scutellaria Lateriflora 15 [hp_X]/1 g; Delphinium Staphisagria Seed 15 [hp_X]/1 g; Datura Stramonium 15 [hp_X]/1 g; Theridion Curassavicum 15 [hp_X]/1 g; Echinacea, Unspecified 8 [hp_X]/1 g; Ginkgo 8 [hp_X]/1 g; Hypericum Perforatum 8 [hp_X]/1 g; Passiflora Incarnata Flowering Top 8 [hp_X]/1 g
INACTIVE INGREDIENTS: Sucrose

Hyperactivity - Mental Focus

INDICATIONS & USAGE SECTION

Hyperactivity - Mental Focus Formulated for symptoms associated with adult attention-deficit and hyperactivity disorders, for emotional balance and mental focus.

DOSAGE & ADMINISTRATION SECTION

Directions: Ages 12 and up, take 6 pellets orally one to four times daily or as directed by a healthcare professional.

ACTIVE INGREDIENT SECTION

Adrenalinum 20x, Tarentula cubensis 20x, Aconitum nap. 15x, Arg. nit. 15x, Arsenicum alb. 15x, Baptisia 15x, Chamomilla 15x, Cypripedium 15x, Digitalis 15x, Gelsemium 15x, Humulus 15x, Ignatia 15x, Impatiens glandulifera flos 15x, Iodium 15x, Lachesis 15x, Lycopodium 15x, Nat. mur. 15x, Nux vom.15x, Scutellaria lateriflora 15x, Staphysag. 15x, Stramonium 15x, Theridion 15x, Echinacea 8x, Gingko 8x, Hypericum 8x, Passiflora 8x, Echinacea 3x, Gingko 3x, Hypericum 3x, Passiflora 3x.

PURPOSE SECTION

Formulated for symptoms associated with adult attention-deficit and hyperactivity disorders, and support for emotional balance and mental focus.

INACTIVE INGREDIENT SECTION

Inactive Ingredients: Gluten-free, non-GMO, beet-derived sucrose pellets.

QUESTIONS? SECTION

www.newtonlabs.net Newton Laboratories, Inc. FDA Est # 1051203 - Conyers, GA 30012
Questions? 1.800.448.7256

WARNINGS SECTION

Warning: Do not use if tamper - evident seal is broken or missing. Consult a licensed healthcare professional if pregnant, nursing or if symptoms worsen or persist for more than a few days. Keep out of reach of children.

PREGNANCY OR BREAST FEEDING SECTION

Consult a licensed healthcare professional if pregnant, nursing or if symptoms worsen or persist for more than a few days.

KEEP OUT OF REACH OF CHILDREN SECTION

Keep out of reach of children.